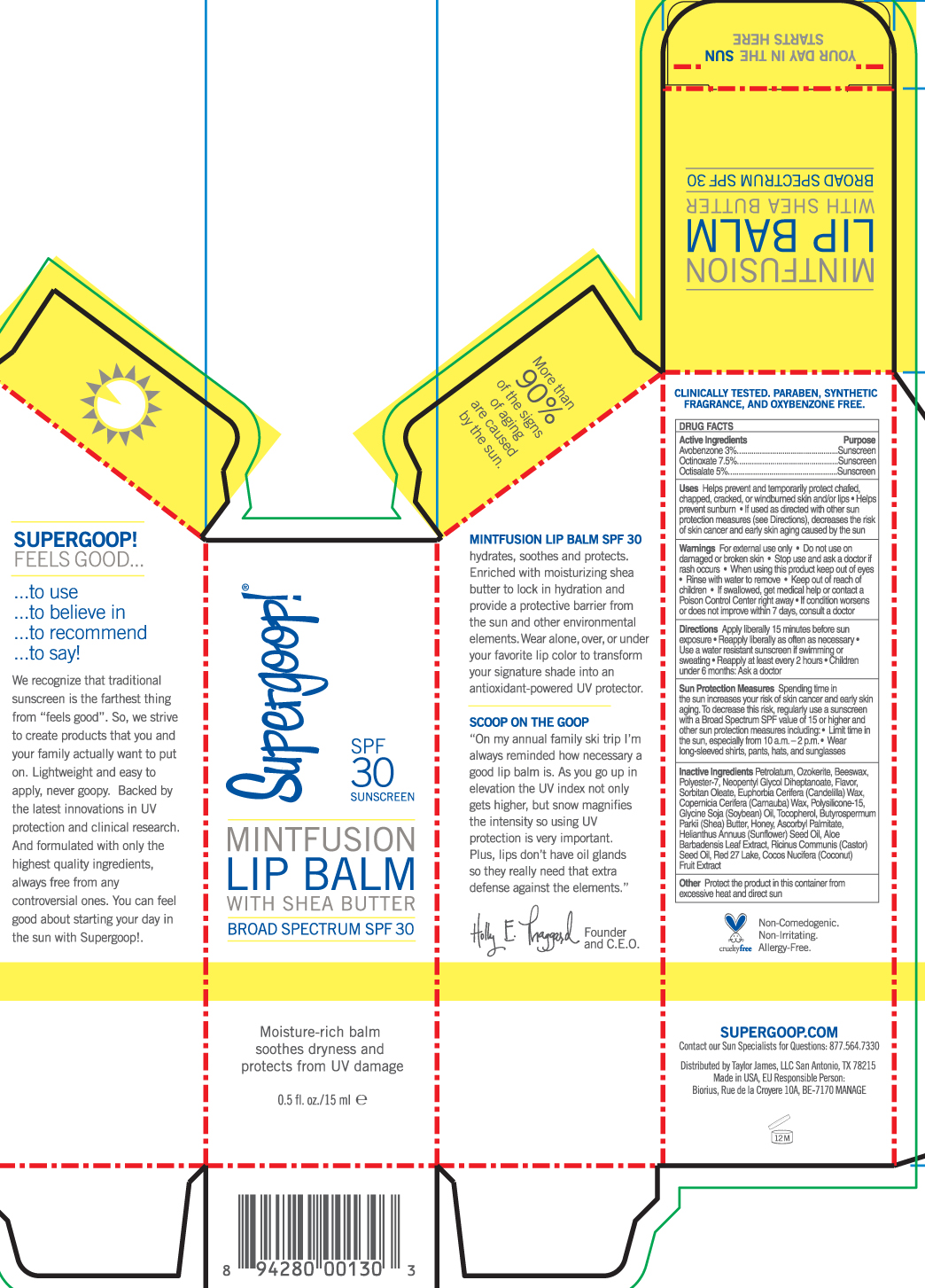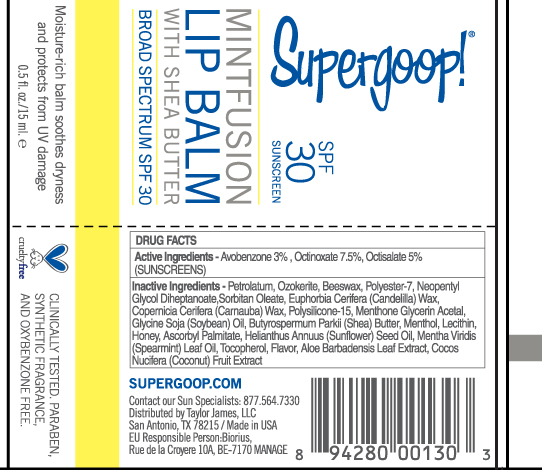 DRUG LABEL: Mint Fusion Lip Balm SPF 30

NDC: 75936-113 | Form: CREAM
Manufacturer: TAYLOR JAMES, LTD.
Category: otc | Type: HUMAN OTC DRUG LABEL
Date: 20201112

ACTIVE INGREDIENTS: OCTINOXATE 1.11 g/15 mL; OCTISALATE 0.74 g/15 mL; AVOBENZONE 0.44 g/15 mL
INACTIVE INGREDIENTS: YELLOW WAX; CERESIN; CANDELILLA WAX; CARNAUBA WAX; HONEY; ASCORBYL PALMITATE; ALOE VERA LEAF; SORBITAN MONOOLEATE; POLYSILICONE-15; TOCOPHEROL; .ALPHA.-TOCOPHEROL ACETATE; MENTHONE 1,2-GLYCEROL KETAL, (-)-; MENTHOL; SPEARMINT OIL; COCONUT OIL

Mint Fusion Lip Balm

Active Ingredients Purpose

Avobenzone 3.0% Sunscreen

Ocinoxate 7.5% Sunscreen

Octisalate 5.0% Sunscreen

PURPOSE

Helps prevent and temporarily protect chafed, chapped, cracked or windburned skin and/or lips. Helps prevent sunburn. If used as directed with other sun protection measures (see Directions) decreases the risk of skin cancer and early skin aging caused by the sun.

Keep out of reach of children

Stop use and ask a doctor if rash occurs

WARNINGS

Warnings For external use only. Do not use on damaged or broken skin. When using this product keep out of eyes.Rinse with water to remove. If swallowed, get medical help or contact a poison control center right away. If condition worsens or does not improve within 7 days, consult a doctor.

Directions

· Apply liberally 15 minutes before sun exposure

-Reapply liberally as often as necessary

· Use a water resistant sunscreen if swimming or sweating

· Children under 6 months: Ask a doctor

Reapply at least every 2 hours

· Sun Protection Measures. Spending time in the sun increases your risk of skin
cancer and early skin aging. To decrease this risk, regularly use a sunscreen
with broad spectrum SPF of 15 or higher and other sun protection measures
including:
· limit time in the sun, especially from 10 a.m. - 2 p.m.

INACTIVE INGREDIENT

Inactive Ingredients- Petrolatum, Ozokerite, Beeswax, Polyester-7, Neopentyl Glycol Diheptanoate, Flavor, Sorbitan Oleate, Euphorbia Cerifera (Candelilla) wax, Copernicia cerifera (carnauba) Wax, Polysiilicone-15, Glycine Soja (Soybean) Oil, Tocopherol, Butyrospermum Parkii (Shea) Butter, Honey, Ascorbyl Palmitate, Helianthus Annuus (Sunflower) Seed Oil, Aloe Barbadensis Leaf Extract, Ricinus Communis (Castor) Seed Oil, Red 27 Lake, Cocos Nucifera (coconut) Fruit Extract

PACKAGE LABEL

Supergoop SPF 30

Soothe

Protect

Hydrate

MintFusion Lip Balm with Shea Butter

.50 Fl Oz